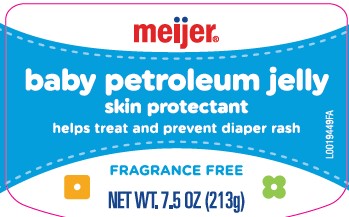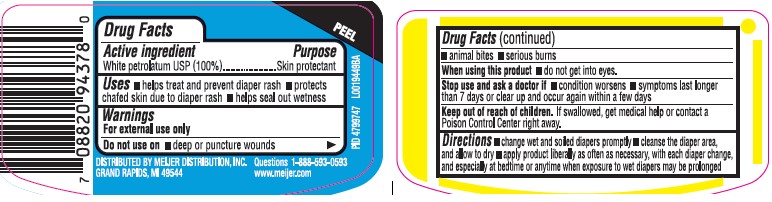 DRUG LABEL: Petroleum
NDC: 79481-0960 | Form: JELLY
Manufacturer: Meijer, Inc.
Category: otc | Type: HUMAN OTC DRUG LABEL
Date: 20260224

ACTIVE INGREDIENTS: PETROLATUM 1 g/1 g

Meijer 960.000/960AA
Baby Petroleum Jelly

Active ingredient

White Petrolatum, USP (100%)

Purpose

Skin Protectant

Use

- helps treat and prevent diaper rash
- protects chafed skin due to diaper rash
- helps seal out wetness

Warnings

For external use only

Do not use on

- deep or puncture wounds
- animal bites
- serious burns

When using this product

- do not get into eyes

Stop use and ask a doctor if

- condition worsens
- systems last longer than 7 days or clear up and occur again within a few days

Keep out of reach of children.

If swallowed, get medical help or contact a Poison Control Center right away.

Directions

- change wet and soiled diapers promptly
- cleanse the diaper area, and allow to dry
- apply product liberally as often as necessary, with each diaper change, and especially at bedtime or anytime when exposure to wet diapers may be prolonged

Inactive ingredients

None

ADVERSE REACTION

DISTRIBUTED BY MEIJER DISTRIBUTION, INC.

GRAND RAPIDS, MI 49544

Questions 1-800-593-0593

www.meijer.com

Principal display panel

meijer®

baby petroleum jelly

skin protectant

helps treat and prevent diaper rash

FRAGRANCE FREE

NET WT. 7.5 OZ (213 g)